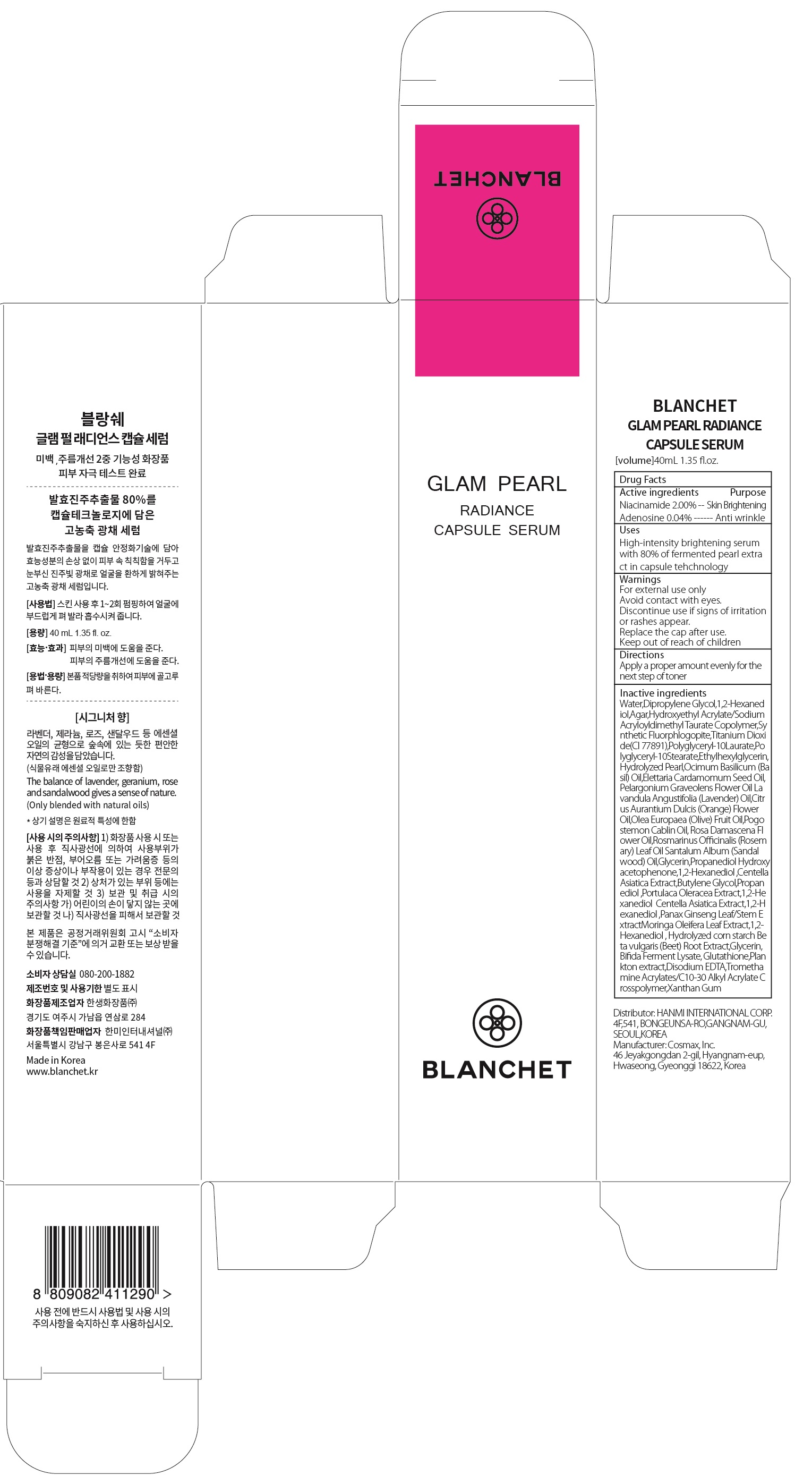 DRUG LABEL: BLANCHET GLAM PEARL RADIANCE CAPSUL E SERUM
NDC: 79171-030 | Form: LIQUID
Manufacturer: Hanmi International Corp.
Category: otc | Type: HUMAN OTC DRUG LABEL
Date: 20200806

ACTIVE INGREDIENTS: Niacinamide 0.8 g/40 mL; Adenosine 0.01 g/40 mL
INACTIVE INGREDIENTS: Water; Dipropylene Glycol; 1,2-Hexanediol

ACTIVE INGREDIENTS

Niacinamide 2.00%
Adenosine 0.04%

PURPOSE

Skin Brightening
Anti wrinkle

Uses

High-intnsity brightening serum with 80% of fermented pearl extract in capsule tehchnology

WARNINGS

For external use only
Avoid contact with eyes.
Discontinue use if signs of irritation or rashes appear.
Replace the cap after use.
Keep out of reach of children

KEEP OUT OF REACH OF CHILDREN

Directions

Apply a proper amount evenly for the next step of toner

INACTIVE INGREDIENTS

Water,Dipropylene Glycol,1,2-Hexanediol,Agar,Hydroxyethyl Acrylate/Sodium Acryloyldimethyl Taurate Copolymer,Synthetic Fluorphlogopite,Titanium Dioxide(CI 77891),Polyglyceryl-10Laurate,Polyglyceryl-10Stearate, Ethylhexylglycerin,Hydrolyzed Pearl,Ocimum Basilicum (Basil) Oil, Elettaria Cardamomum Seed Oil,Pelargonium Graveolens Flower Oil, Lavandula Angustifolia (Lavender) Oil,Citrus Aurantium Dulcis (Orange) Flower Oil,Olea Europaea (Olive) Fruit Oil,Pogostemon Cablin Oil, Rosa Damascena Flower Oil,Rosmarinus Officinalis (Rosemary) Leaf Oil, Santalum Album (Sandalwood) Oil,Water,Glycerin,Propanediol, Hydroxyacetophenone,1,2-Hexanediol ,Centella Asiatica Extract,Butylene Glycol,Propanediol ,Portulaca Oleracea Extract,1,2-Hexanediol, Centella Asiatica Extract,1,2-Hexanediol ,Panax Ginseng Leaf/Stem Extract,
Moringa Oleifera Leaf Extract,1,2-Hexanediol , Hydrolyzed corn starch, Beta vulgaris (Beet) Root Extract,Glycerin,Bifida Ferment Lysate,
Glutathione,Plankton extract,Disodium EDTA,Tromethamine, Acrylates/C10-30 Alkyl Acrylate Crosspolymer,Xanthan Gum